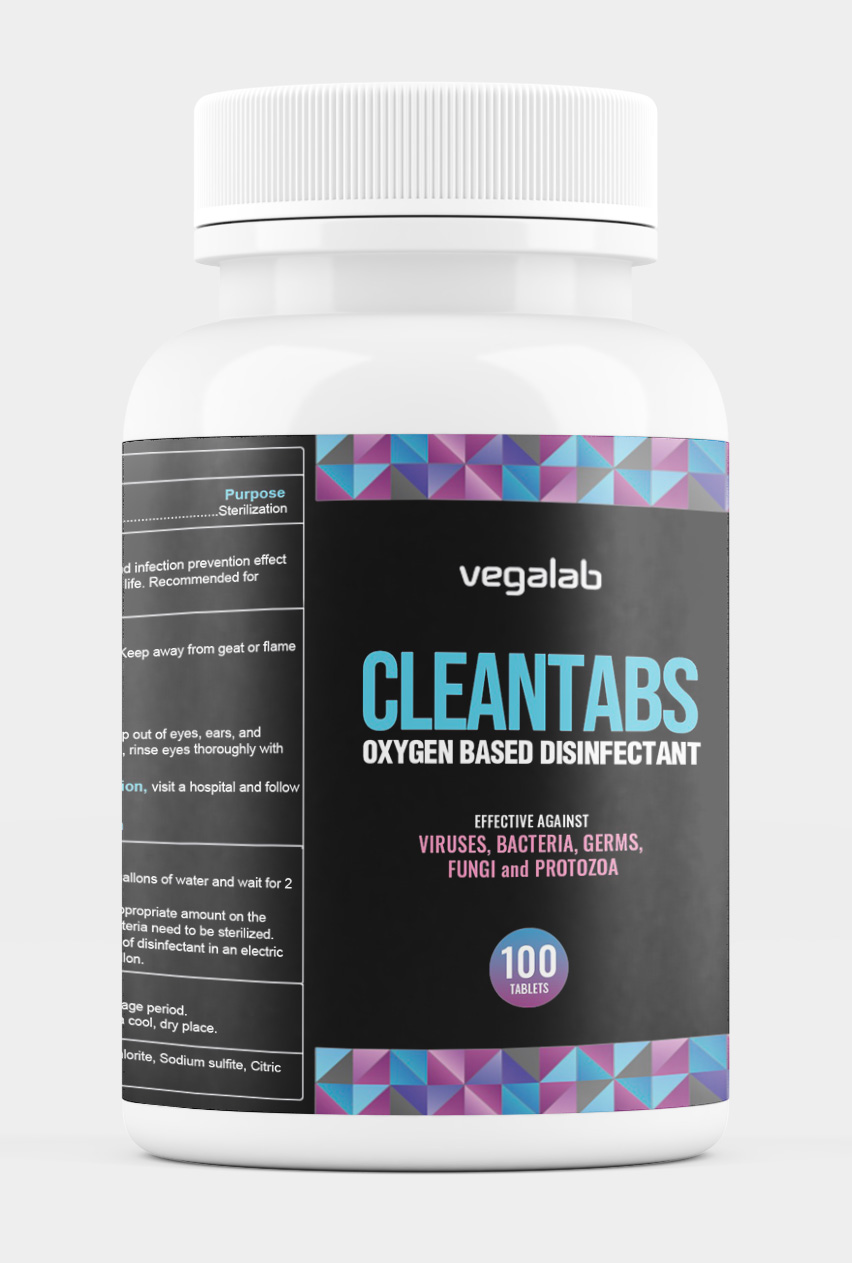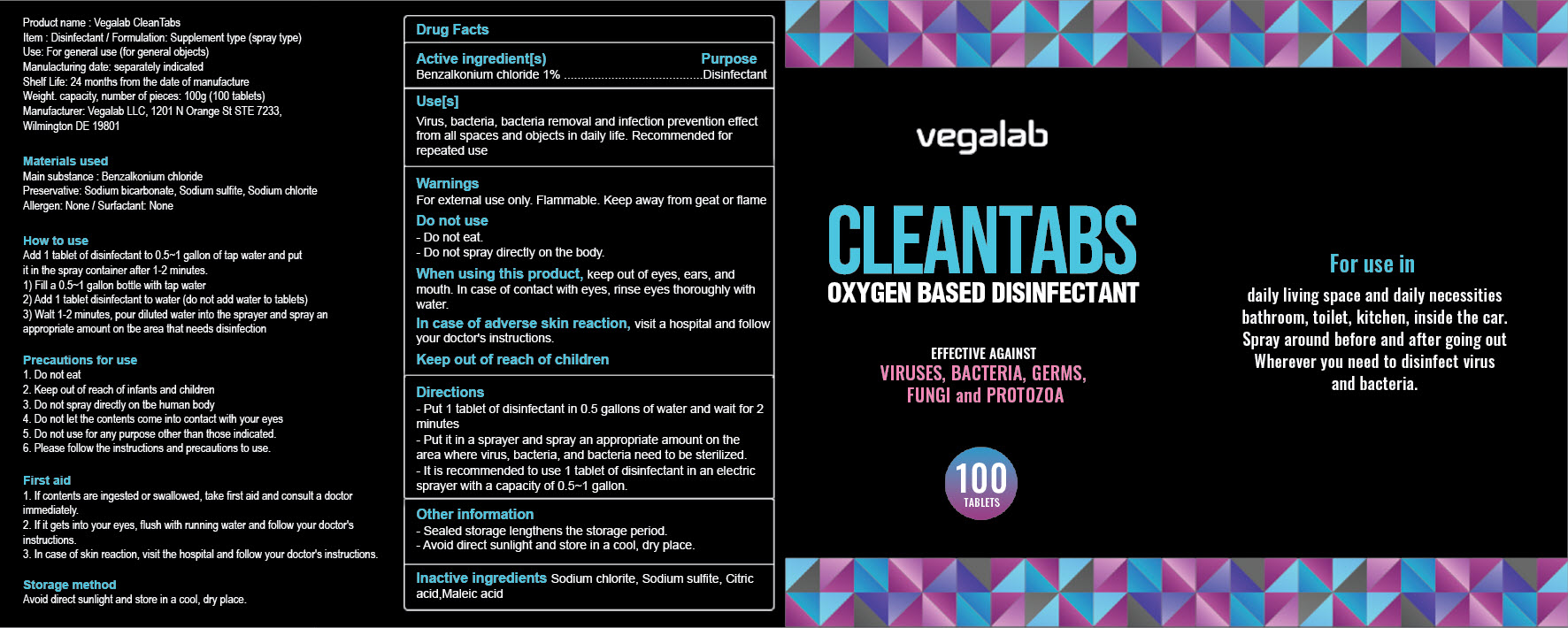 DRUG LABEL: Vegalab CleanTabs
NDC: 85289-101 | Form: TABLET, SOLUBLE
Manufacturer: Vegalab LLC
Category: otc | Type: HUMAN OTC DRUG LABEL
Date: 20250304

ACTIVE INGREDIENTS: BENZALKONIUM CHLORIDE 1 g/100 g
INACTIVE INGREDIENTS: SODIUM CHLORITE; MALEIC ACID; CITRIC ACID MONOHYDRATE; SODIUM SULFITE

Active Ingredient(s)

Sodium bicarbonate 60%

Purpose:

Hand Sanitizer

How to Use

Add 1 tablet of disinfection to 0.5~1 gallon of tap water and put it in the spray container after 1-2 minutes.

1) Fill a 0.5~1 gallon of bottle with tap water

2) Add 1 tablet disinfectant to water (do not add water to tablets)

3) Wait 1-2 minutes, pour diluted water into the sprayer and spray an appropriate amount on the area that needs disinfection.

Precautions for use:

1. Do not eat

2. Keep out of reach of infants and children

3. Do not spray directly on tbe human body
4. Do not let the contents come into contact with your eyes
5. Do not use for any purpose other than those indicated.
6. Please follow the instructions and precautions to use.

First aid:
1. If contents are ingested or swallowed, take first aid and consult a doctor immediately.
2. If it gets into your eyes, flush with running water and follow your doctor's instructions.
3. In case of skin reaction, visit the hospital and follow your doctor's instructions.

Storage method:

Avoid direct sunlight and store in a cool, dry place.

Warning:

For external use only. Flammable. Keep away from geat or flame

Do not use:

- Do not eat.
- Do not spray directly on the body.

When using this product:

keep out of eyes, ears, and mouth. In case of contact with eyes, rinse eyes thoroughly with water.

Keep out of reach of children:

In case of adverse skin reaction:

visit a hospital and follow your doctor's instructions.

Directions

- Put 1 tablet of disinfectant in 0.5 gallons of water and wait for 2 minutes
- Put it in a sprayer and spray an appropriate amount on the area where virus, bacteria, and bacteria need to be sterilized.
- Sealed storage lengthens the storage period.
- Avoid direct sunlight and store in a cool, dry place.
- It is recommended to use 1 tablet of disinfectant in an electric sprayer with a capacity of 0.5~1 gallon.

Other information:

- Sealed storage lengthens the storage period.
- Avoid direct sunlight and store in a cool, dry place.

Inactive ingredients

Sodium chlorite, Sodium sulfite, Citric acid,Maleic acid

Indication & Usage:

Virus, bacteria, bacteria removal and infection prevention effect from all spaces and objects in daily life. Recommended for repeated use.